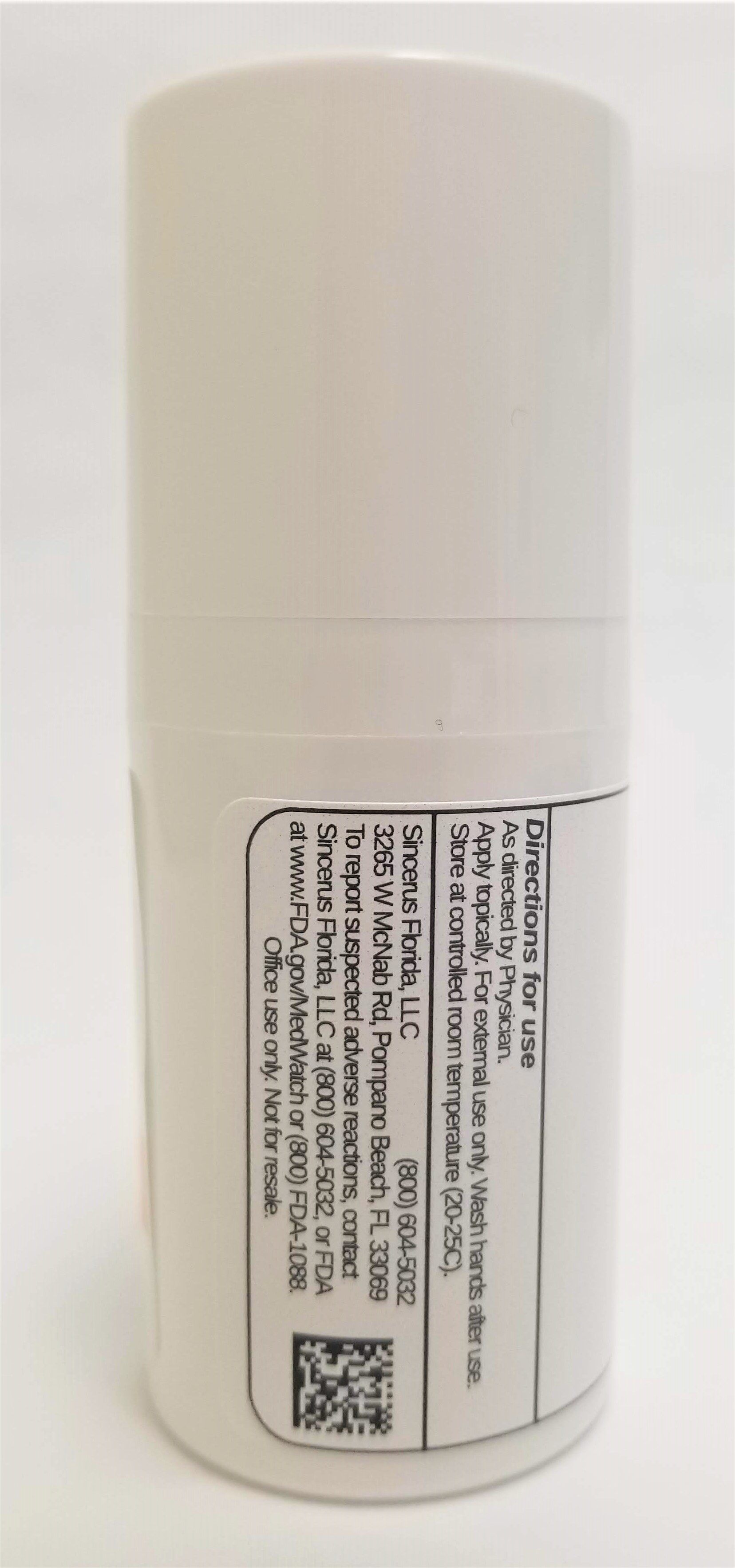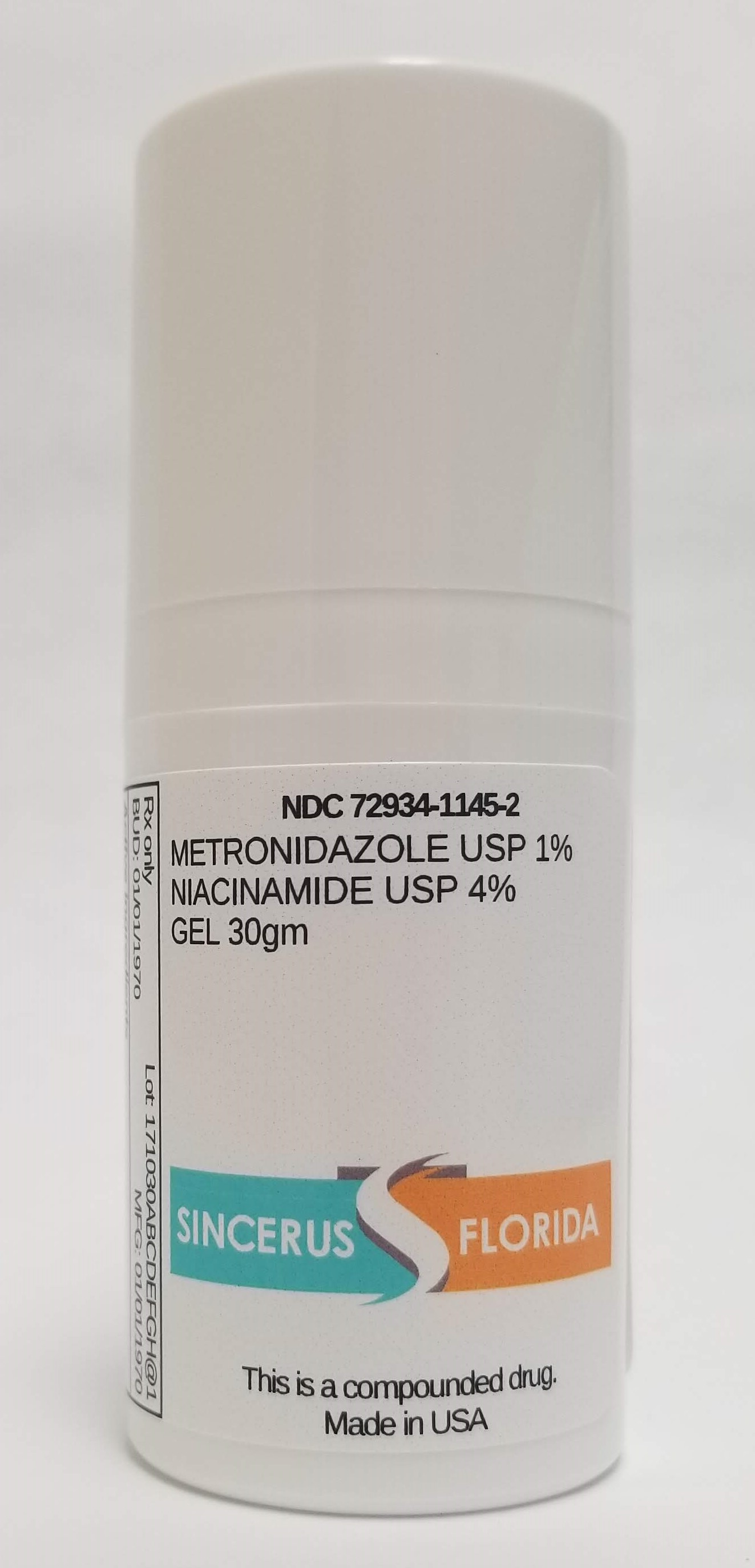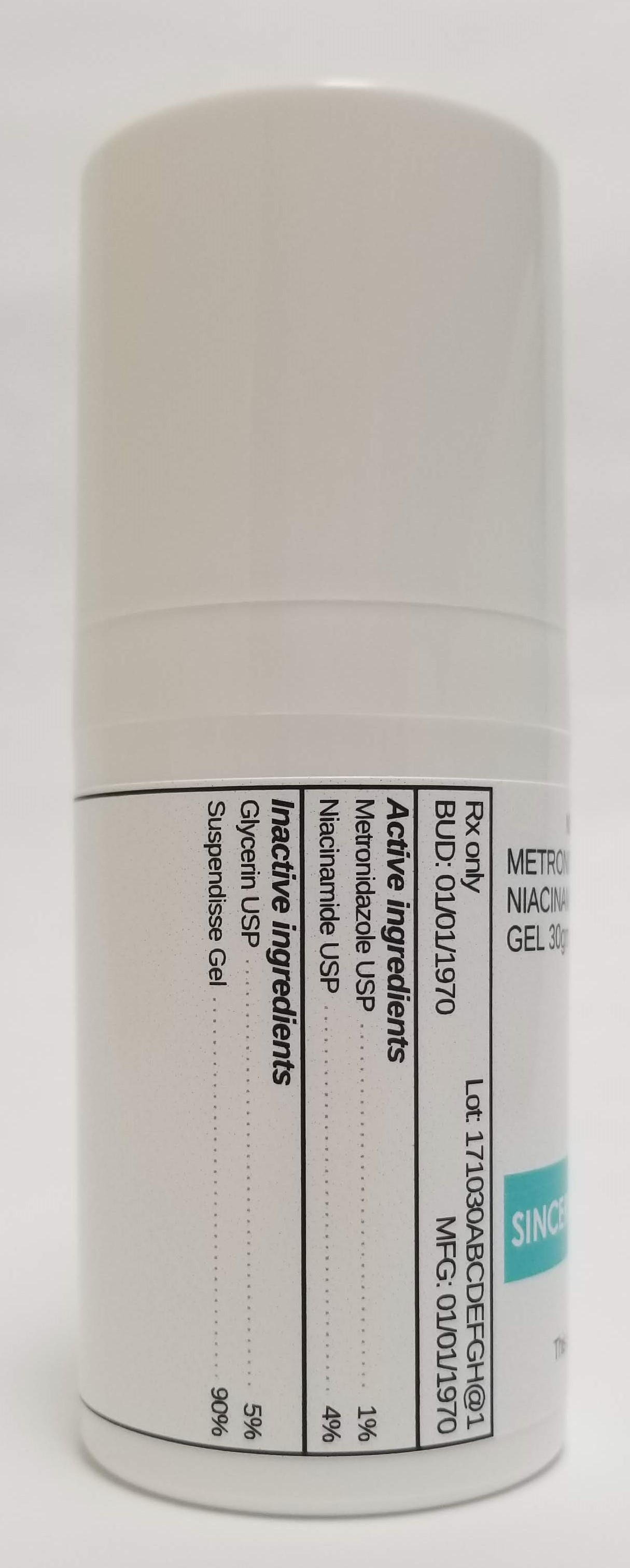 DRUG LABEL: METRONIDAZOLE 1% / NIACINAMIDE 4%
NDC: 72934-1145 | Form: GEL
Manufacturer: Sincerus Florida, LLC
Category: prescription | Type: HUMAN PRESCRIPTION DRUG LABEL
Date: 20190515

ACTIVE INGREDIENTS: METRONIDAZOLE 1 g/100 g; NIACINAMIDE 4 g/100 g

METRONIDAZOLE 1% / NIACINAMIDE 4%